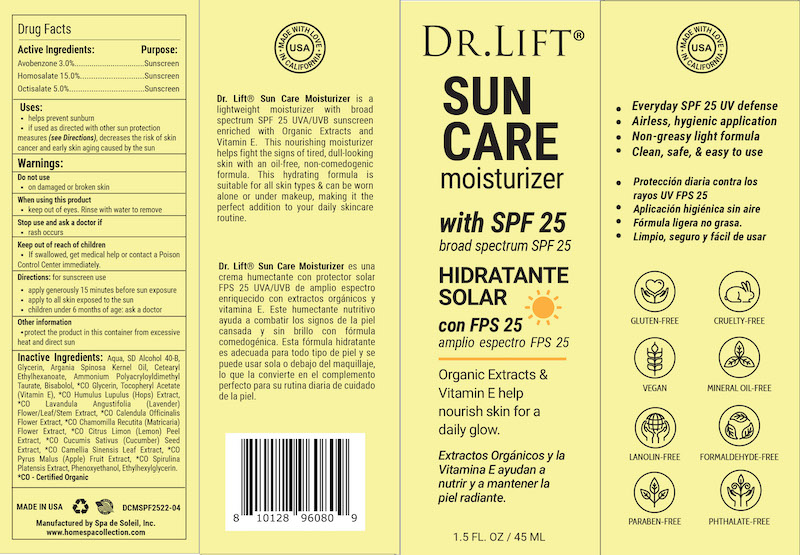 DRUG LABEL: Dr Lift Sun Care SPF 25
NDC: 68062-8821 | Form: LOTION
Manufacturer: Spa de Soleil
Category: otc | Type: HUMAN OTC DRUG LABEL
Date: 20260121

ACTIVE INGREDIENTS: OCTISALATE 2.25 mg/45 mL; AVOBENZONE 1.35 mg/45 mL; HOMOSALATE 6.75 mg/45 mL
INACTIVE INGREDIENTS: ARGANIA SPINOSA SEED; GLYCERIN; CETEARYL ETHYLHEXANOATE; ALCOHOL; WATER

Dr Lift Sun Care SPF 25

Active Ingredients

Avobenzone 3.0%

Homosalate 15.0%

Octisalatae 5.0%

Purpose

Sunscreen

Warnings

- Do not use on damaged or broken skin

When using this product

- Keep out of eyes. Rinse with water to remove

Stop use and ask a doctor if

- rash occurs

Keep out of reach of children

- If swallowed, get medical help or contact a Poison Control Center immediately

Directions

Directions: for sunscreen use

. apply generously 15 minutes before sun exposure

. apply to all skin exposed to the sun

. children under 6 months of age: ask a doctor

Inactive Ingredients

Inactive Ingredients: Aqua, SD Alcohol 40-B, Glycerin, Argania Spinosa Kernel Oil, Cetearyl Ethylhexanoate, Ammonium Polyacryloyldimethyl Taurate, Bisabolol, *CO Glycerin, Tocopheryl Acetate (Vitamin E), *CO Humulus Lupulus (Hops) Extract, *CO Lavandula Angustifolia (Lavender) Flower/Leaf/Stem Extract, *CO Calendula Officinalis Flower Extract, *CO Chamomilla Recutita (Matricaria) Flower Extract, *CO Citrus Limon (Lemon) Peel Extract, *CO Cucumis Sativus (Cucumber) Seed Extract, *CO Camellia Sinensis Leaf Extract, *CO Pyrus Malus (Apple) Fruit Extract, *CO Spirulina Platensis Extract, Phenoxyethanol, Ethylhexylglycerin.

*CO - Certified Organic

Keep out of reach of children

INDICATIONS AND USAGE

Directions: for sunscreen use

. apply generously 15 minutes before sun exposure

. apply to all skin exposed to the sun

. children under 6 months of age: ask a doctor

Other information

.protect the product in this container from excessive heat and direct sun